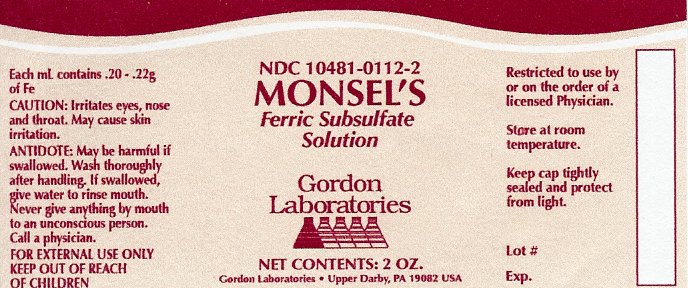 DRUG LABEL: MONSELS SOLUTION
NDC: 10481-0112 | Form: LIQUID
Manufacturer: Gordon Laboratories
Category: prescription | Type: HUMAN PRESCRIPTION DRUG LABEL
Date: 20111207

ACTIVE INGREDIENTS: FERRIC SUBSULFATE .21 g/1 g

MONSELS SOLUTION

HOW SUPPLIED

Light-resistant 2 ml bottles.

INDICATIONS AND USAGE

Used as a styptic in its undiluted form.

WARNINGS AND PRECAUTIONS

It should not be used in vesicular, bullous, or exudative (oozing) dermatoses because it may then cause permanent pigmentation on the skin. May be harmful if swallowed. For external use only. If swallowed, do not induce vomiting unless directed to do so by medical personnel. Never give anything by mouth to an unconscious person. Loosen tight clothing such as a collar, tie, belt or waistband. Get medical attention immediately. Keep out of reach of children.

Restricted to use by or on the order of a licensed Physician. Store at room temperature. Keep cap tightly sealed and protect from light.